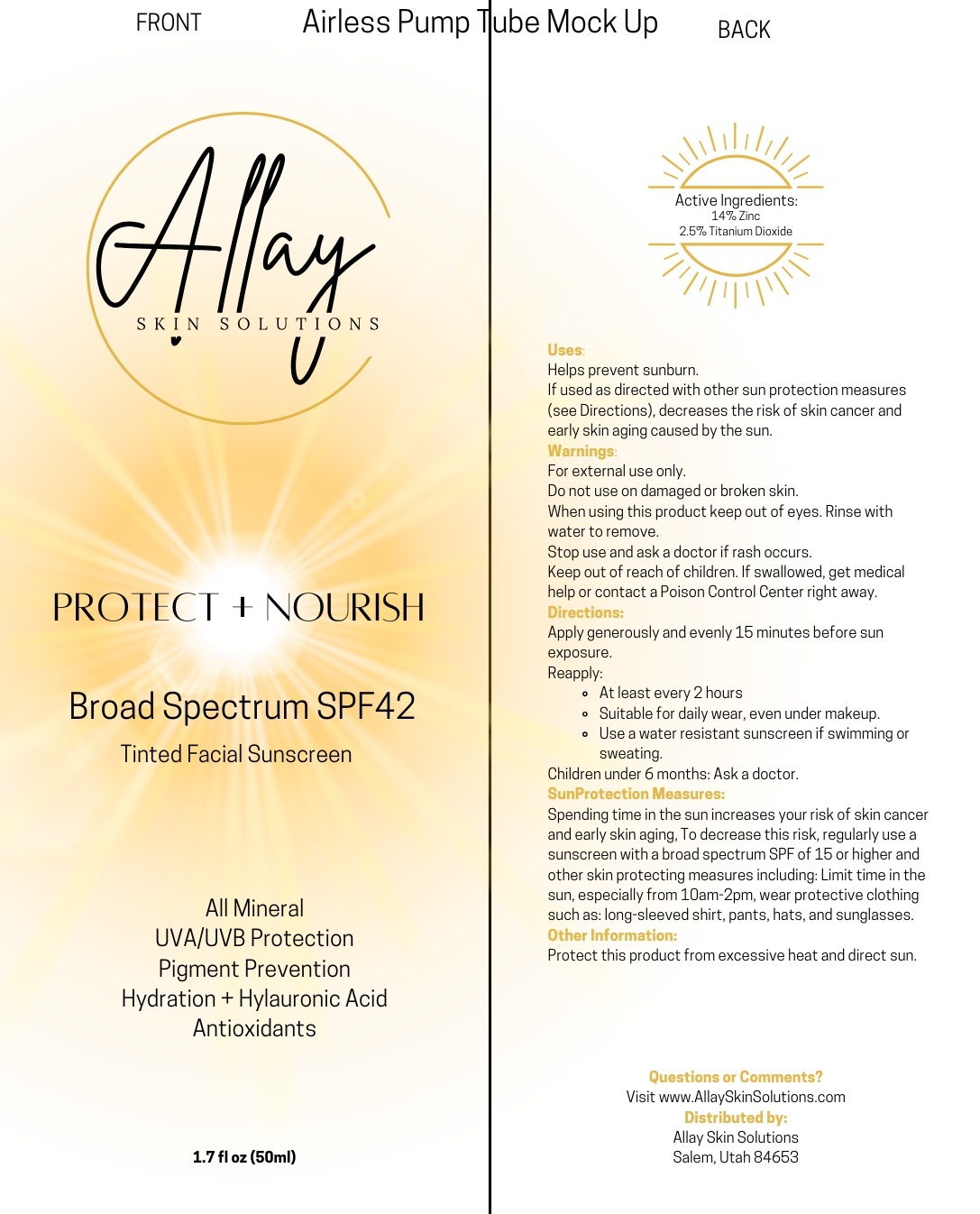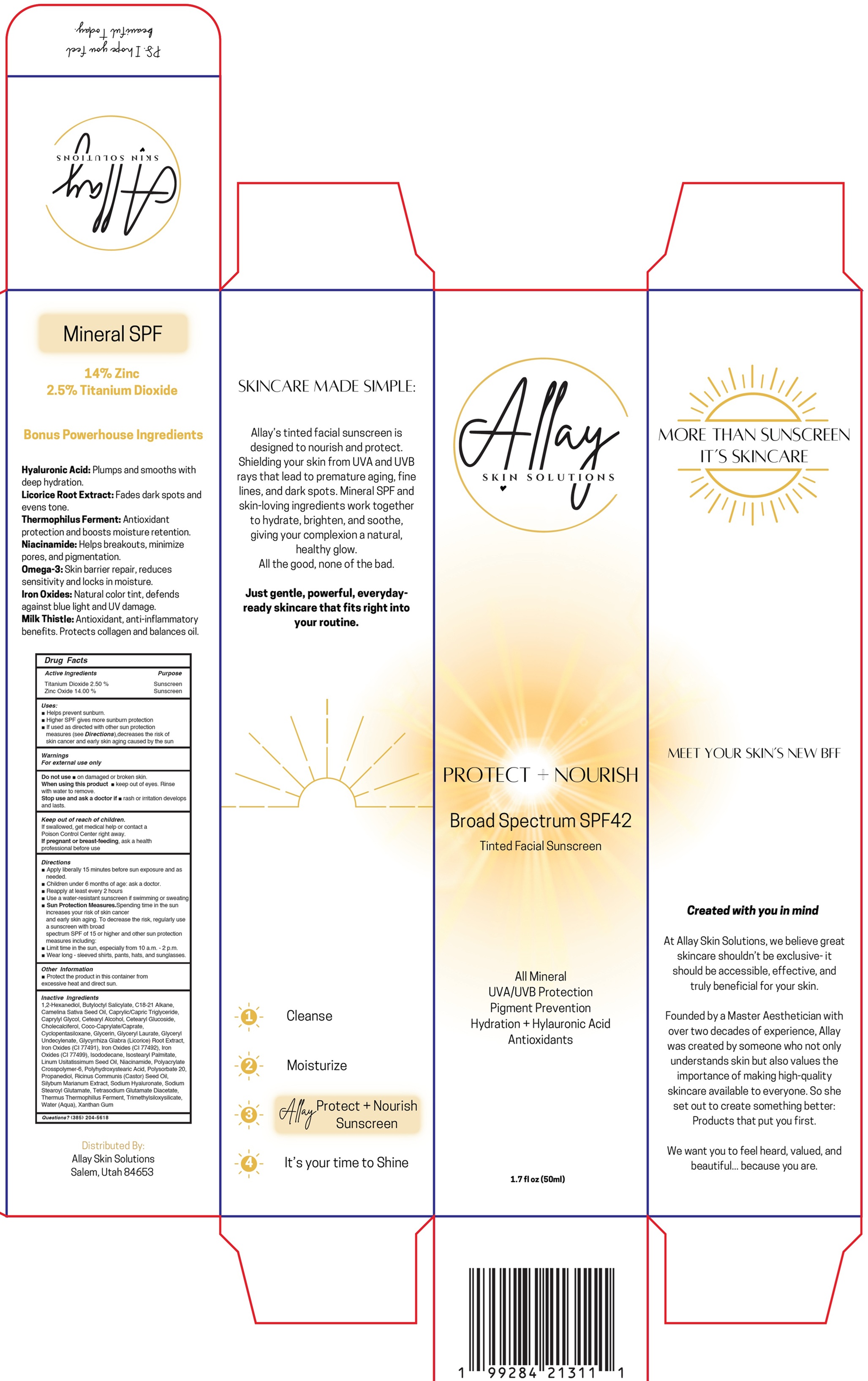 DRUG LABEL: Allay Skin Solutions Protect Nourish Mineral Sunscreen SPF 42
NDC: 87419-978 | Form: CREAM
Manufacturer: ALLAY SKIN SOLUTIONS LLC
Category: otc | Type: HUMAN OTC DRUG LABEL
Date: 20260218

ACTIVE INGREDIENTS: TITANIUM DIOXIDE 25 mg/1 mL; ZINC OXIDE 140 mg/1 mL
INACTIVE INGREDIENTS: 1,2-HEXANEDIOL; BUTYLOCTYL SALICYLATE; C18-C21 ALKANE; CAMELINA SATIVA SEED OIL; MEDIUM-CHAIN TRIGLYCERIDES; CAPRYLYL GLYCOL; CETOSTEARYL ALCOHOL; CETEARYL GLUCOSIDE; CHOLECALCIFEROL; COCOYL CAPRYLOCAPRATE; CYCLOMETHICONE 5; GLYCERIN; GLYCERYL LAURATE; GLYCYRRHIZA GLABRA (LICORICE) ROOT POWDER; FERRIC OXIDE RED; FERRIC OXIDE YELLOW; FERROSOFERRIC OXIDE; ISODODECANE; ISOSTEARYL PALMITATE; NIACINAMIDE; AMMONIUM ACRYLOYLDIMETHYLTAURATE, DIMETHYLACRYLAMIDE, LAURYL METHACRYLATE AND LAURETH-4 METHACRYLATE COPOLYMER, TRIMETHYLOLPROPANE TRIACRYLATE CROSSLINKED (45000 MPA.S); POLYSORBATE 20; PROPANEDIOL; CASTOR OIL; MILK THISTLE; HYALURONATE SODIUM; SODIUM STEAROYL GLUTAMATE; TETRASODIUM GLUTAMATE DIACETATE; WATER; XANTHAN GUM

Allay Skin Solutions Protect Nourish Mineral Sunscreen SPF 42

Active Ingredients

Titanium Dioxide 2.50 %

Zinc Oxide 14.00 %

Purpose

Sunscreen

Uses:

- Helps prevent sunburn
- Higher SPF gives more sunburn protection
- If used as directed with other sun protection measures (see Directions),decreases the risk of skin cancer and early skin aging caused by the sun

Warnings

For external use only

Do not use

- on damaged or broken skin.

When using this product

- keep out of eyes. Rinse with water to remove

Stop use and ask a doctor if

- rash or irritation develops and lasts.

Keep out of reach of children

If swallowed, get medical help or contact a Poison Control Center right away

If pregnant or breast-feeding,

ask a health professional before use

Directions

- Apply liberally 15 minutes before sun exposure and as needed.
- Children under 6 months of age: ask a doctor.
- Reapply at least every 2 hours
- Use a water-resistant sunscreen if swimming or sweating
- Sun Protection Measures.Spending time in the sun increases your risk of skin cancer and early skin aging. To decrease the risk, regularly use a sunscreen with broad spectrum SPF of 15 or higher and other sun protection measures including:

- Limit time in the sun, especially from 10 a.m. - 2 p.m.
- Wear long - sleeved shirts, pants, hats, and sunglasses

Other Information

- Protect the product in this container from excessive heat and direct sun.

Inactive Ingredients

1,2-Hexanediol, Butyloctyl Salicylate, C18-21 Alkane, Camelina Sativa Seed Oil, Caprylic/Capric Triglyceride, Caprylyl Glycol, Cetearyl Alcohol, Cetearyl Glucoside, Cholecalciferol, Coco-Caprylate/Caprate, Cyclopentasiloxane, Glycerin, Glyceryl Laurate, Glyceryl Undecylenate, Glycyrrhiza Glabra (Licorice) Root Extract , Iron Oxides (CI 77491), Iron Oxides (CI 77492), Iron Oxides (CI 77499), Isododecane, Isostearyl Palmitate, Linum Usitatissimum Seed Oil, Niacinamide, Polyacrylate Crosspolymer-6, Polyhydroxystearic Acid, Polysorbate 20, Propanediol, Ricinus Communis (Castor) Seed Oil, Silybum Marianum Extract, Sodium Hyaluronate, Sodium Stearoyl Glutamate, Tetrasodium Glutamate Diacetate, Thermus Thermophillus Ferment, Trimethylsiloxysilicate,Water (Aqua), Xanthan Gum

Questions?

(385) 204-5618